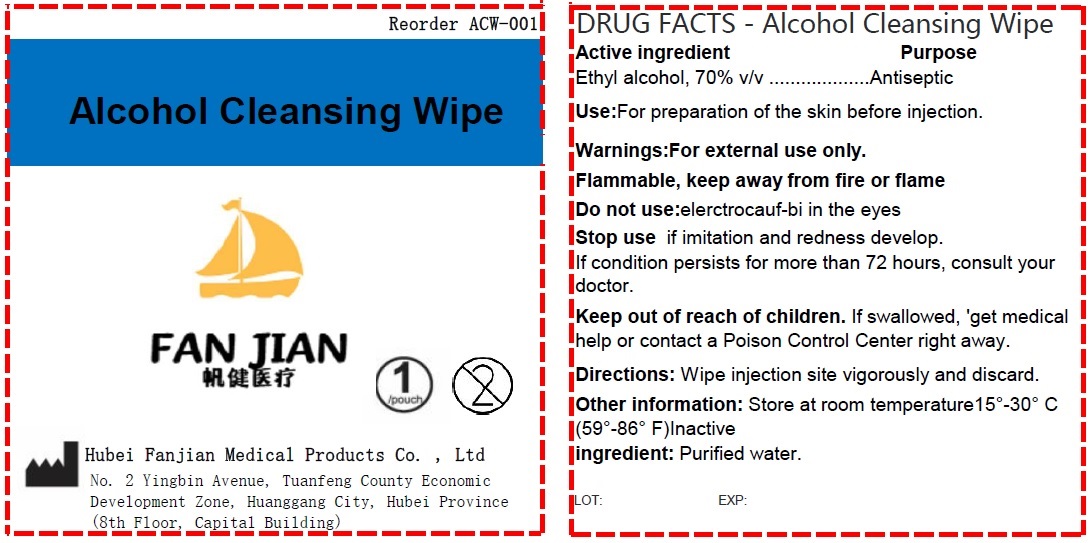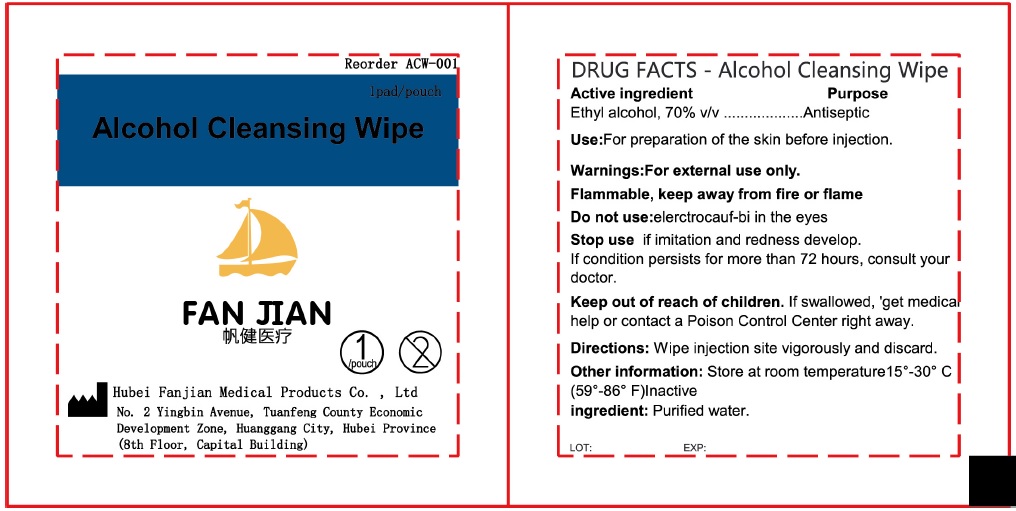 DRUG LABEL: Alcohol Cleansing Wipe
NDC: 83165-001 | Form: CLOTH
Manufacturer: Hubei Fanjian Medical Product Co.,Ltd
Category: otc | Type: HUMAN OTC DRUG LABEL
Date: 20231110

ACTIVE INGREDIENTS: ALCOHOL 0.7 mL/1 mL
INACTIVE INGREDIENTS: WATER

Alcohol Cleansing Wipe

Active ingredients

Ethyl alcohol 62% v/v

Purpose

`Antiseptic

Use

For preparation of the skin before injection.

Warnings:

For external use only.

Flammable, keep away from fire or flame

Do not use:

elerctrocauf-bi in the eyes

Stop use

if imitation and redness develop. If condition persists for more than 72 hours, consult your doctor.

Keep out of reach of children.

If swallowed, get medical help or contact a Poison Control Center right away.

Directions:

Wipe injection site vigorously and discard.

Other information:

Store at room temperature15°-30° C (59°-86° F)

Inactive ingredients

Purified water.